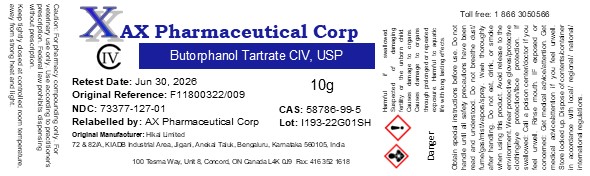 DRUG LABEL: Butorphanol Tartrate
NDC: 73377-107 | Form: POWDER
Manufacturer: AX Pharmaceutical Corp
Category: other | Type: BULK INGREDIENT - ANIMAL DRUG
Date: 20230616
DEA Schedule: CIV

ACTIVE INGREDIENTS: BUTORPHANOL TARTRATE 1 g/1 g

Butorphanol Tartrate